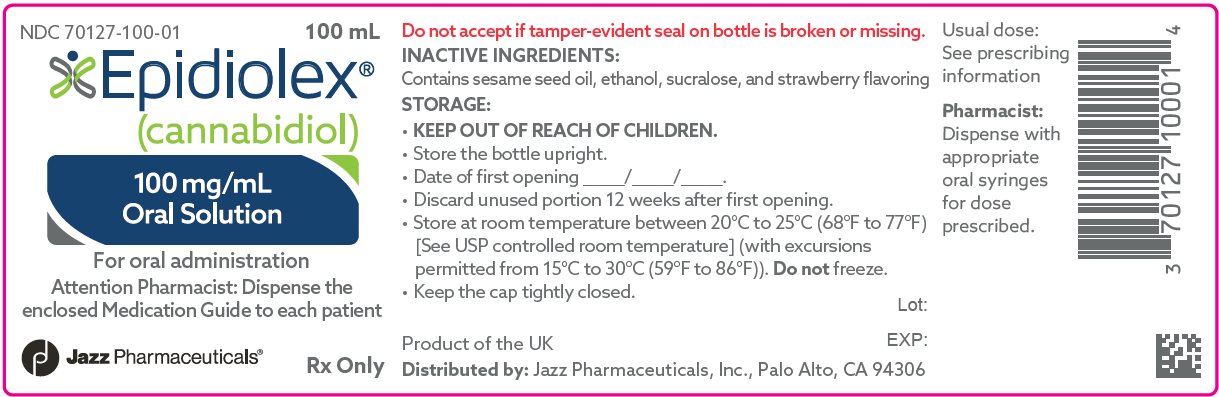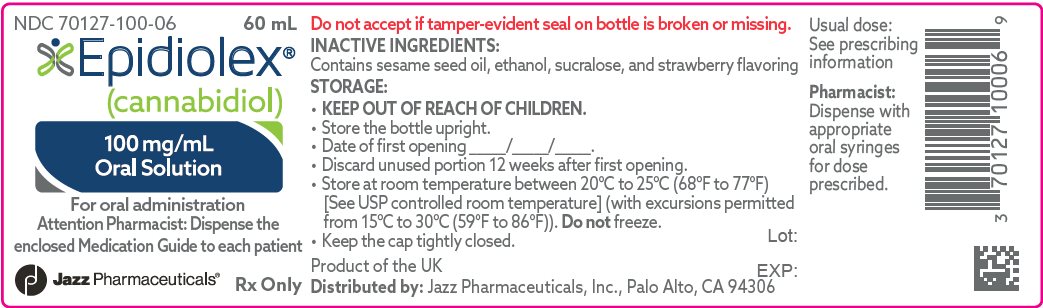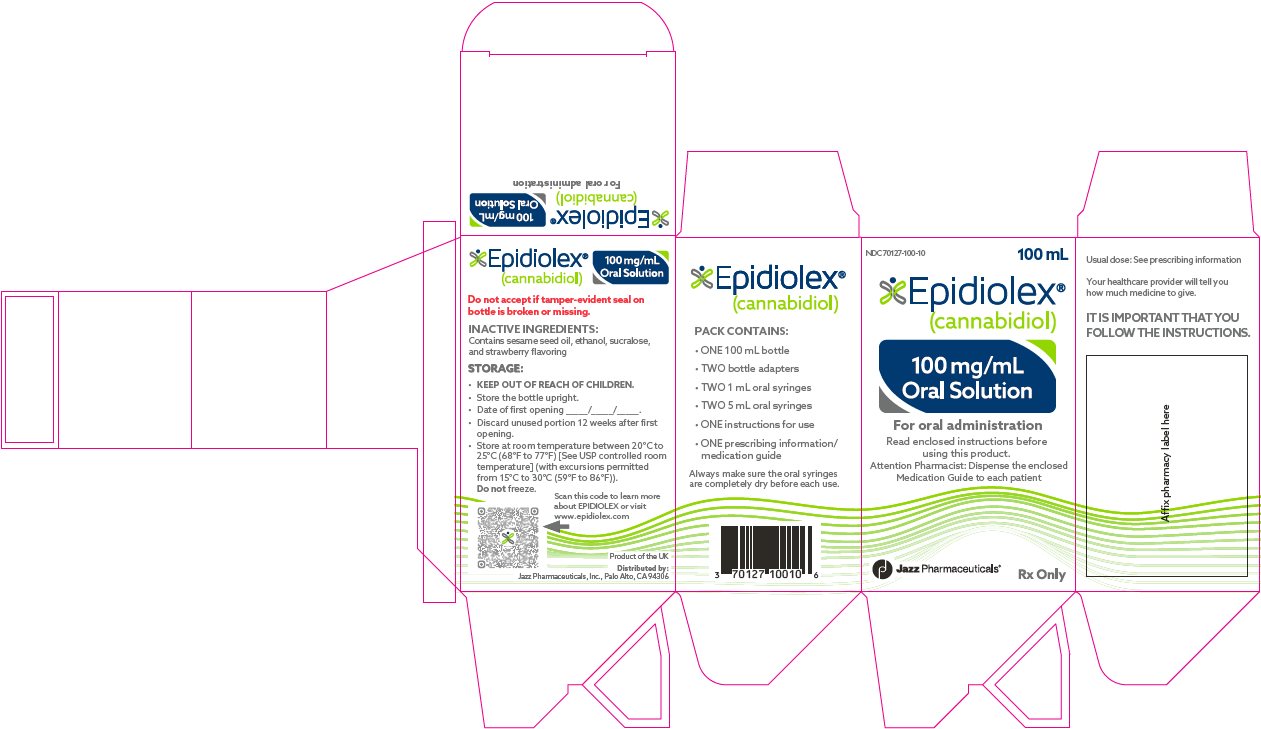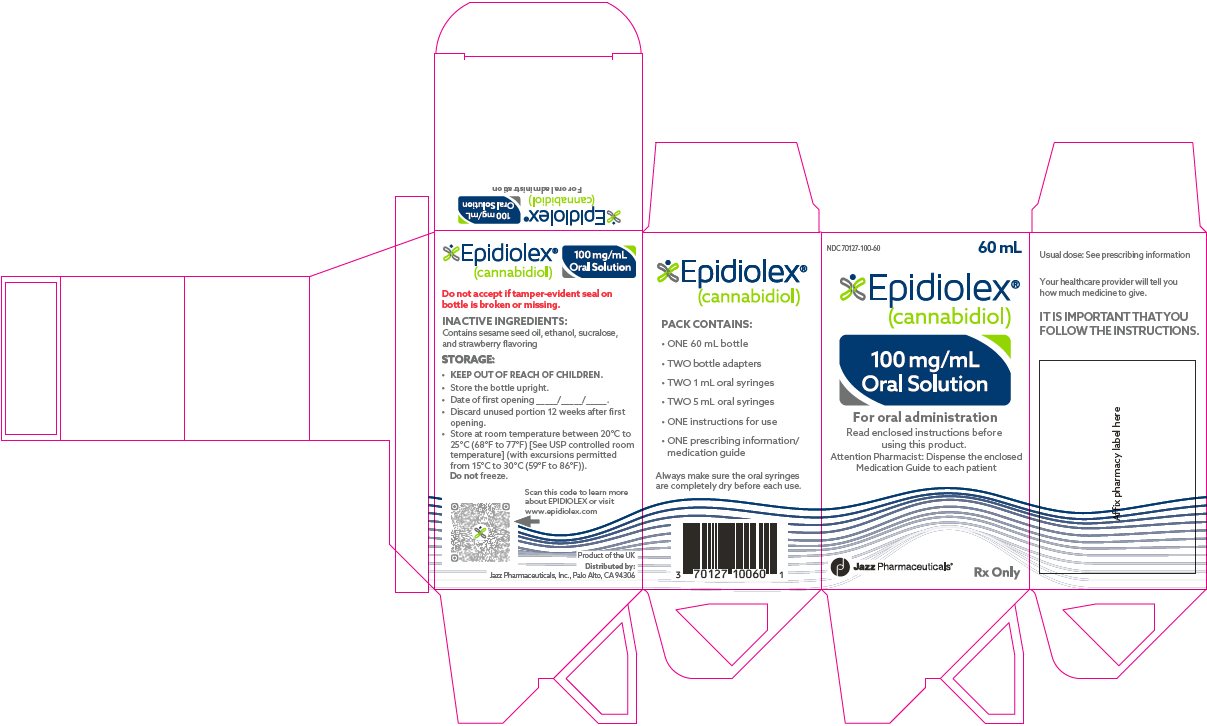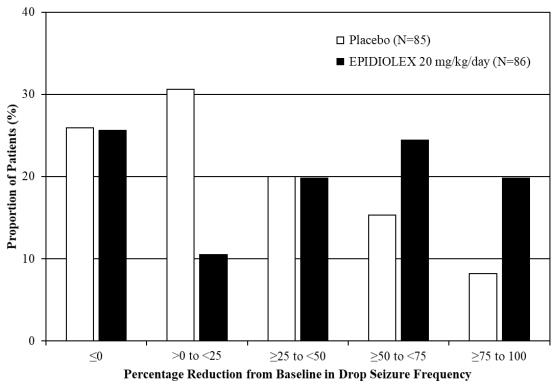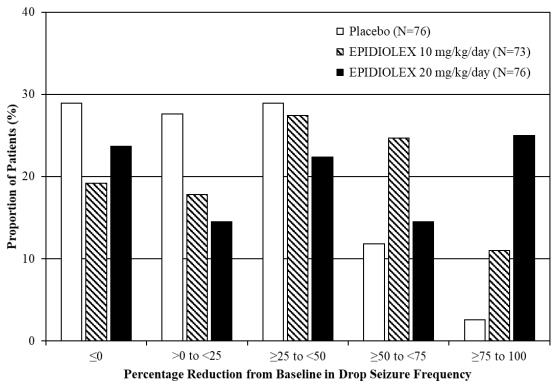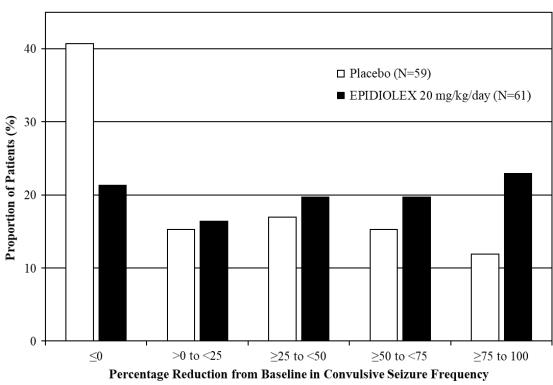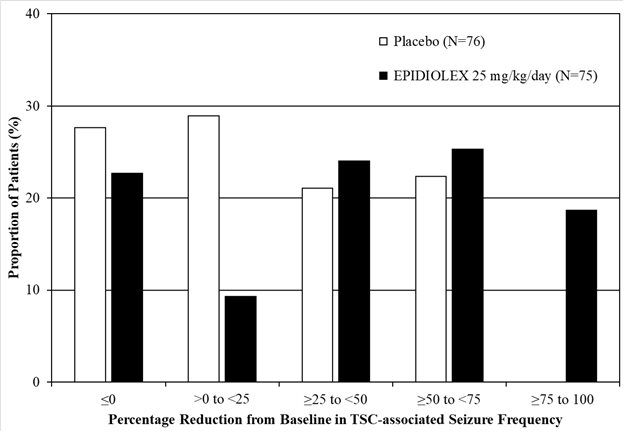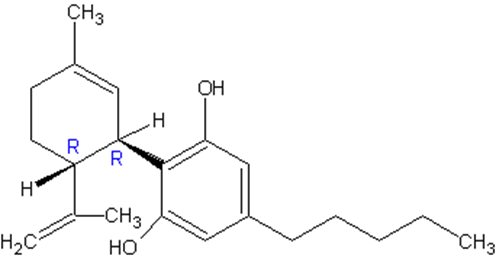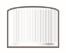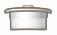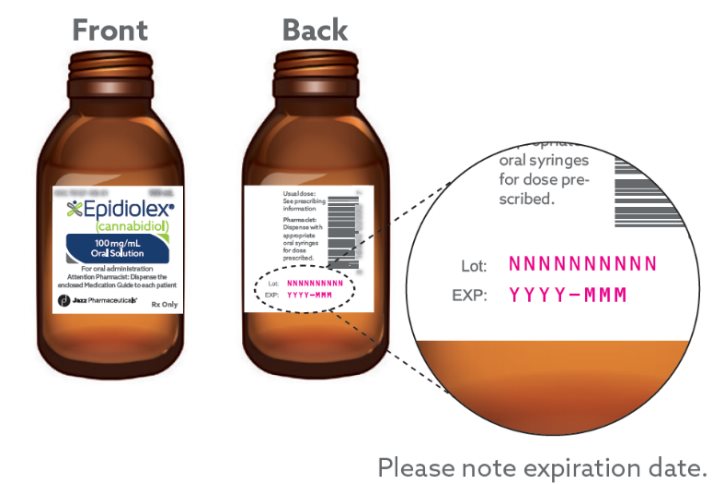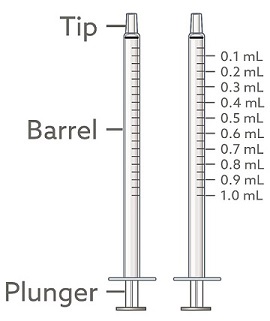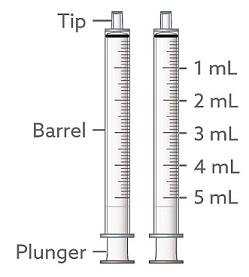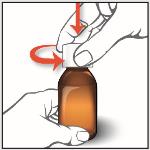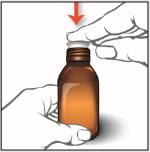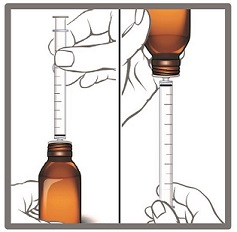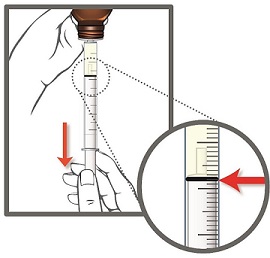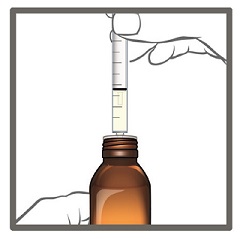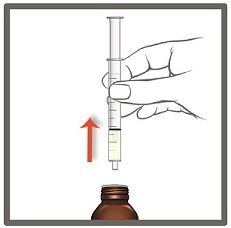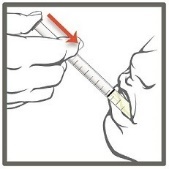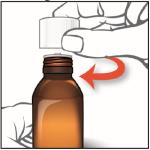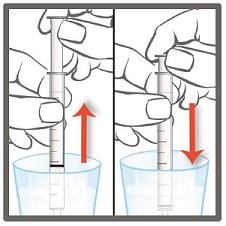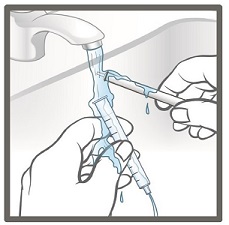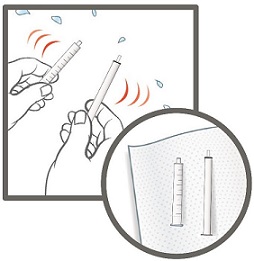 DRUG LABEL: Epidiolex
NDC: 70127-100 | Form: SOLUTION
Manufacturer: Jazz Pharmaceuticals, Inc.
Category: prescription | Type: HUMAN PRESCRIPTION DRUG LABEL
Date: 20250731

ACTIVE INGREDIENTS: CANNABIDIOL 100 mg/1 mL
INACTIVE INGREDIENTS: SESAME OIL; ALCOHOL; SUCRALOSE; STRAWBERRY

HIGHLIGHTS OF PRESCRIBING INFORMATION

These highlights do not include all the information needed to use EPIDIOLEX® safely and effectively. See full prescribing information for EPIDIOLEX.
EPIDIOLEX® (cannabidiol) oral solution
Initial U.S. Approval: 2018

1 INDICATIONS AND USAGE

EPIDIOLEX is indicated for the treatment of seizures associated with Lennox-Gastaut syndrome, Dravet syndrome, or tuberous sclerosis complex in patients 1 year of age and older (1)

2 DOSAGE AND ADMINISTRATION

- Obtain serum transaminases (ALT and AST) and total bilirubin levels in all patients prior to starting treatment. (2.1, 5.1)
- See Full Prescribing Information for titration. (2.2, 2.3)

Seizures Associated with Lennox-Gastaut Syndrome or Dravet Syndrome

- The recommended starting dosage is 2.5 mg/kg by mouth twice daily (5 mg/kg/day). After one week, the dosage can be increased to a maintenance dosage of 5 mg/kg twice daily (10 mg/kg/day). (2.2)
- Based on individual clinical response and tolerability, EPIDIOLEX can be increased up to a maximum recommended maintenance dosage of 10 mg/kg twice daily (20 mg/kg/day).

Seizures Associated with Tuberous Sclerosis Complex

- The recommended starting dosage is 2.5 mg/kg by mouth twice daily (5 mg/kg/day). Increase the dose weekly by 2.5 mg/kg twice daily (5 mg/kg/day), as tolerated, to a recommended maintenance dosage of 12.5 mg/kg twice daily (25 mg/kg/day). (2.3)

Patients with Impaired Hepatic Function

- Dosage adjustment is recommended for patients with moderate or severe hepatic impairment. (2.6, 8.6)

3 DOSAGE FORMS AND STRENGTHS

Oral solution: 100 mg/mL (3)

4 CONTRAINDICATIONS

Hypersensitivity to cannabidiol or any of the ingredients in EPIDIOLEX (4)

5 WARNINGS AND PRECAUTIONS

- Hepatic Injury: EPIDIOLEX can cause transaminase elevations. Concomitant use of valproate and higher doses of EPIDIOLEX increase the risk of transaminase elevations. See Full Prescribing Information for serum transaminase and bilirubin monitoring recommendations. (5.1)
- Somnolence and Sedation: Monitor for somnolence and sedation and advise patients not to drive or operate machinery until they have gained sufficient experience on EPIDIOLEX. (5.2)
- Suicidal Behavior and Ideation: Monitor patients for suicidal behavior and thoughts. (5.3)
- Hypersensitivity Reactions: Advise patients to seek immediate medical care. Discontinue and do not restart EPIDIOLEX if hypersensitivity occurs. (5.4)
- Withdrawal of Antiepileptic Drugs: EPIDIOLEX should be gradually withdrawn to minimize the risk of increased seizure frequency and status epilepticus. (5.5)

6 ADVERSE REACTIONS

The most common adverse reactions (10% or more for EPIDIOLEX and greater than placebo) in patients with Lennox-Gastaut syndrome or Dravet syndrome are: somnolence; decreased appetite; diarrhea; transaminase elevations; fatigue, malaise, and asthenia; rash; insomnia, sleep disorder, and poor quality sleep; and infections. (6.1)

The most common adverse reactions (10% or more for EPIDIOLEX and greater than placebo) in patients with tuberous sclerosis complex are: diarrhea; transaminase elevations; decreased appetite; somnolence; pyrexia; and vomiting. (6.1)

To report SUSPECTED ADVERSE REACTIONS, contact Jazz Pharmaceuticals, Inc. at 1-800-520-5568 or FDA at 1-800-FDA-1088 or www.fda.gov/medwatch.

7 DRUG INTERACTIONS

- Strong inducer of CYP3A4 or CYP2C19: Consider dose increase of EPIDIOLEX. (7.1)
- Consider a dose reduction of substrates of CYP1A2, CYP2C8, UGT1A9, and orally administered P-gp substrates. (7.2)
- A lower starting dose of orally administered everolimus is recommended. (7.2)
- Consider dose modification of CYP2B6 or CYP2C19 substrates. (7.2)

8 USE IN SPECIFIC POPULATIONS

Pregnancy: Based on animal data, may cause fetal harm. (8.1)

FULL PRESCRIBING INFORMATION

1 INDICATIONS AND USAGE

EPIDIOLEX is indicated for the treatment of seizures associated with Lennox-Gastaut syndrome (LGS), Dravet syndrome (DS), or tuberous sclerosis complex (TSC) in patients 1 year of age and older.

2 DOSAGE AND ADMINISTRATION

2.1 Assessments Prior to Initiating EPIDIOLEX

Because of the risk of hepatocellular injury, obtain serum transaminases (ALT and AST) and total bilirubin levels in all patients prior to starting treatment with EPIDIOLEX [see Warnings and Precautions (5.1)].

2.2 Dosing for Seizures Associated with Lennox-Gastaut Syndrome or Dravet Syndrome

- The starting dosage is 2.5 mg/kg by mouth twice daily (5 mg/kg/day).
- After one week, the dosage can be increased to a maintenance dosage of 5 mg/kg twice daily (10 mg/kg/day).
- Patients who are tolerating EPIDIOLEX at 5 mg/kg twice daily and require further reduction of seizures may benefit from a dosage increase up to a maximum recommended maintenance dosage of 10 mg/kg twice daily (20 mg/kg/day), in weekly increments of 2.5 mg/kg twice daily (5 mg/kg/day), as tolerated. For patients in whom a more rapid titration from 10 mg/kg/day to 20 mg/kg/day is warranted, the dosage may be increased no more frequently than every other day. Administration of the 20 mg/kg/day dosage resulted in somewhat greater reductions in seizure rates than the recommended maintenance dosage of 10 mg/kg/day, but with an increase in adverse reactions.

2.3 Dosing for Seizures Associated with Tuberous Sclerosis Complex

- The starting dosage is 2.5 mg/kg by mouth twice daily (5 mg/kg/day).
- Increase the dose in weekly increments of 2.5 mg/kg twice daily (5 mg/kg/day), as tolerated, to a recommended maintenance dosage of 12.5 mg/kg twice daily (25 mg/kg/day). For patients in whom a more rapid titration to 25 mg/kg/day is warranted, the dosage may be increased no more frequently than every other day.
- The effectiveness of doses lower than 12.5 mg/kg twice daily has not been studied in patients with TSC.

2.4 Administration Instructions

Food may affect EPIDIOLEX levels [see Clinical Pharmacology (12.3)]. Consistent dosing of EPIDIOLEX with respect to meals is recommended to reduce variability in cannabidiol plasma exposure.

Calibrated measuring devices (1 mL and 5 mL oral syringes) will be provided and are recommended to measure and deliver the prescribed dose accurately [see How Supplied/Storage and Handling (16.1)]. A household teaspoon or tablespoon is not an adequate measuring device.

Oral administration is recommended. When necessary, EPIDIOLEX can be enterally administered via silicone feeding tubes, such as nasogastric or gastrostomy tubes. The recommended volume for flushing (with room temperature drinking water) after each dose is approximately 5 times the priming volume of the tube. The flushing volume may need to be modified in patients with fluid restrictions. Do not use with tubes made of polyvinyl chloride (PVC) or polyurethane and avoid use of silicone nasogastric tubes with short lengths and narrow diameters (e.g., less than 50 cm and less than 5 FR).

Discard any unused EPIDIOLEX remaining 12 weeks after first opening the bottle [see How Supplied/ Storage and Handling (16.2)].

2.5 Discontinuation of EPIDIOLEX

When discontinuing EPIDIOLEX, the dose should be decreased gradually. As with most antiepileptic drugs, abrupt discontinuation should be avoided when possible, to minimize the risk of increased seizure frequency and status epilepticus [see Warnings and Precautions (5.5)].

2.6 Patients with Hepatic Impairment

Dose adjustment is recommended in patients with moderate (Child-Pugh B) hepatic impairment or severe (Child-Pugh C) hepatic impairment [see Warnings and Precautions (5.1), Use in Specific Populations (8.6), and Clinical Pharmacology (12.3)]. It may be necessary to have slower dose titration in patients with moderate or severe hepatic impairment than in patients without hepatic impairment (see Table 1).

EPIDIOLEX does not require dose adjustment in patients with mild (Child-Pugh A) hepatic impairment.

Table 1: Dose Adjustments in Patients with Hepatic Impairment
Hepatic Impairment | Starting Dosage | In Patients with LGS or DS | In Patients with TSC
Hepatic Impairment | Starting Dosage | Maintenance Dosage Range | Maintenance Dosage
Mild | 2.5 mg/kg twice daily (5 mg/kg/day) | 5 to 10 mg/kg twice daily (10 to 20 mg/kg/day) | 12.5 mg/kg twice daily (25 mg/kg/day)
Moderate | 1.25 mg/kg twice daily; (2.5 mg/kg/day) | 2.5 to 5 mg/kg twice daily (5 to 10 mg/kg/day) | 6.25 mg/kg twice daily (12.5 mg/kg/day)
Severe | 0.5 mg/kg twice daily (1 mg/kg/day) | 1 to 2 mg/kg twice daily (2 to 4 mg/kg/day) | 2.5 mg/kg twice daily (5 mg/kg/day)

3 DOSAGE FORMS AND STRENGTHS

Cannabidiol oral solution: 100 mg/mL of a strawberry-flavored, clear, colorless to yellow solution.

4 CONTRAINDICATIONS

EPIDIOLEX is contraindicated in patients with a history of hypersensitivity to cannabidiol or any of the ingredients in the product [see Description (11) and Warnings and Precautions (5.4)].

5 WARNINGS AND PRECAUTIONS

5.1 Hepatic Injury

EPIDIOLEX can cause dose-related elevations of liver transaminases (alanine aminotransferase [ALT] and/or aspartate aminotransferase [AST]). In controlled studies for LGS and DS (10 and 20 mg/kg/day dosages) and TSC (25 mg/kg/day), the incidence of ALT elevations above 3 times the upper limit of normal (ULN) was 13% (10 and 20 mg/kg/day dosages) and 12% (25 mg/kg/day dosage) in EPIDIOLEX-treated patients compared with 1% in patients on placebo. Less than 1% of EPIDIOLEX-treated patients had ALT or AST levels greater than 20 times the ULN. There were cases of transaminase elevations associated with hospitalization in patients taking EPIDIOLEX. In clinical trials, serum transaminase elevations typically occurred in the first two months of treatment initiation; however, there were some cases observed up to 18 months after initiation of treatment, particularly in patients taking concomitant valproate. Resolution of transaminase elevations occurred with discontinuation of EPIDIOLEX or reduction of EPIDIOLEX and/or concomitant valproate in about two-thirds of the cases. In about one-third of the cases, transaminase elevations resolved during continued treatment with EPIDIOLEX, without dose reduction.

In the postmarketing setting, cases of cholestatic or mixed patterns of liver injury (i.e., based on calculated ratio of [ALT/ULN]/[ALP/ULN] less than 2 and between 2-5, respectively) were reported in patients treated with EPIDIOLEX.

Risk Factors for Transaminase Elevation

Concomitant Valproate and Clobazam

The majority of ALT elevations in the controlled studies occurred in patients taking concomitant valproate [see Drug Interactions (7.3)]. Concomitant use of clobazam also increased the incidence of transaminase elevations, although to a lesser extent than valproate [see Drug Interactions (7.2)]. In EPIDIOLEX-treated patients with LGS or DS (10 and 20 mg/kg/day dosages), the incidence of ALT elevations greater than 3 times the ULN was 30% in patients taking both concomitant valproate and clobazam, 21% in patients taking concomitant valproate (without clobazam), 4% in patients taking concomitant clobazam (without valproate), and 3% in patients taking neither drug. In EPIDIOLEX-treated patients with TSC (25 mg/kg/day), the incidence of ALT elevations greater than 3 times the ULN was 20% in patients taking both concomitant valproate and clobazam, 25% in patients taking concomitant valproate (without clobazam), 0% in patients taking concomitant clobazam (without valproate), and 6% in patients taking neither drug.

Consider discontinuation or dose adjustment of valproate or clobazam if liver enzyme elevations occur.

In the postmarketing setting, cases of elevated ammonia levels were reported in some EPIDIOLEX-treated patients who also had transaminase elevations; where data were available, most cases reported concomitant use of valproate, clobazam, or both. Consider discontinuation or dose adjustment of valproate or clobazam if ammonia level elevations occur.

Dose

Transaminase elevations are generally dose-related. In patients with DS or LGS (10 and 20 mg/kg/day) or TSC (25 mg/kg/day), ALT elevations greater than 3 times the ULN were reported in 17% and 12% of patients taking EPIDIOLEX 20 or 25 mg/kg/day, respectively, compared with 1% in patients taking EPIDIOLEX 10 mg/kg/day. The risk of ALT elevations was higher (25%) in patients with TSC receiving a dosage above the recommended maintenance dosage of 25 mg/kg/day in Study 4.

Baseline Transaminase Elevations

Patients with baseline transaminase levels above the ULN had higher rates of transaminase elevations when taking EPIDIOLEX. In the DS and LGS controlled trials (Studies 1, 2, and 3) in patients taking EPIDIOLEX 20 mg/kg/day, the frequency of treatment-emergent ALT elevations greater than 3 times the ULN was 30% when ALT was above the ULN at baseline, compared to 12% when ALT was within the normal range at baseline. No patients taking EPIDIOLEX 10 mg/kg/day experienced ALT elevations greater than 3 times the ULN when ALT was above the ULN at baseline, compared with 2% of patients in whom ALT was within the normal range at baseline. In the TSC controlled trial (Study 4) in patients taking EPIDIOLEX 25 mg/kg/day, the frequency of treatment-emergent ALT elevations greater than 3 and 5 times the ULN were both 11% when ALT was above the ULN at baseline, compared to 12% and 6%, respectively, when ALT was within the normal range at baseline.

Monitoring

In general, transaminase elevations of greater than 3 times the ULN in the presence of elevated bilirubin without an alternative explanation are an important predictor of severe liver injury. Early identification of elevated liver enzymes may decrease the risk of a serious outcome. Patients with elevated baseline transaminase levels above 3 times the ULN, accompanied by elevations in bilirubin above 2 times the ULN, should be evaluated prior to initiation of EPIDIOLEX treatment.

Prior to starting treatment with EPIDIOLEX, obtain serum transaminases (ALT and AST) and total bilirubin levels. Serum transaminases and total bilirubin levels should be obtained at 1 month, 3 months, and 6 months after initiation of treatment with EPIDIOLEX, and periodically thereafter or as clinically indicated. Serum transaminases and total bilirubin levels should also be obtained within 1 month following changes in EPIDIOLEX dosage and addition of or changes in medications that are known to impact the liver. Consider more frequent monitoring of serum transaminases and bilirubin in patients who are taking valproate or who have elevated liver enzymes at baseline.

If a patient develops clinical signs or symptoms suggestive of hepatic dysfunction (e.g., unexplained nausea, vomiting, right upper quadrant abdominal pain, fatigue, anorexia, or jaundice and/or dark urine), promptly measure serum transaminases and total bilirubin and interrupt or discontinue treatment with EPIDIOLEX, as appropriate. Discontinue EPIDIOLEX in any patients with elevations of transaminase levels greater than 3 times the ULN and bilirubin levels greater than 2 times the ULN. Patients with sustained transaminase elevations of greater than 5 times the ULN should also have treatment discontinued. Patients with prolonged elevations of serum transaminases should be evaluated for other possible causes. Consider dosage adjustment of any coadministered medication that is known to affect the liver (e.g., valproate and clobazam).

5.2 Somnolence and Sedation

EPIDIOLEX can cause somnolence and sedation. In controlled studies for LGS and DS (10 and 20 mg/kg/day dosages), the incidence of somnolence and sedation (including lethargy) was 32% in EPIDIOLEX-treated patients (27% and 34% of patients taking EPIDIOLEX 10 or 20 mg/kg/day, respectively), compared with 11% in patients on placebo and was generally dose-related. The rate was higher in patients on concomitant clobazam (46% in EPIDIOLEX-treated patients taking clobazam compared with 16% in EPIDIOLEX-treated patients not on clobazam). In the controlled study for TSC, the incidence of somnolence and sedation (including lethargy) was 19% in EPIDIOLEX-treated patients (25 mg/kg/day), compared with 17% in patients on placebo. The rate was higher in patients on concomitant clobazam (33% in EPIDIOLEX-treated patients taking clobazam compared with 14% in EPIDIOLEX-treated patients not on clobazam). In general, these effects were more common early in treatment and may diminish with continued treatment. Other CNS depressants, including alcohol, could potentiate the somnolence and sedation effect of EPIDIOLEX. Prescribers should monitor patients for somnolence and sedation and should advise patients not to drive or operate machinery until they have gained sufficient experience on EPIDIOLEX to gauge whether it adversely affects their ability to drive or operate machinery.

5.3 Suicidal Behavior and Ideation

Antiepileptic drugs (AEDs), including EPIDIOLEX, increase the risk of suicidal thoughts or behavior in patients taking these drugs for any indication. Patients treated with an AED for any indication should be monitored for the emergence or worsening of depression, suicidal thoughts or behavior, or any unusual changes in mood or behavior.

Pooled analyses of 199 placebo-controlled clinical trials (mono- and adjunctive therapy) of 11 different AEDs showed that patients randomized to one of the AEDs had approximately twice the risk (adjusted Relative Risk 1.8, 95% CI:1.2, 2.7) of suicidal thinking or behavior compared to patients randomized to placebo. In these trials, which had a median treatment duration of 12 weeks, the estimated incidence rate of suicidal behavior or ideation among 27863 AED-treated patients was 0.43%, compared to 0.24% among 16029 placebo-treated patients, representing an increase of approximately one case of suicidal thinking or behavior for every 530 patients treated. There were four suicides in drug-treated patients in the trials and none in placebo-treated patients, but the number is too small to allow any conclusion about drug effect on suicide.

The increased risk of suicidal thoughts or behavior with AEDs was observed as early as 1 week after starting drug treatment with AEDs and persisted for the duration of treatment assessed. Because most trials included in the analysis did not extend beyond 24 weeks, the risk of suicidal thoughts or behavior beyond 24 weeks could not be assessed.

The risk of suicidal thoughts or behavior was generally consistent among drugs in the data analyzed. The finding of increased risk with AEDs of varying mechanisms of action and across a range of indications suggests that the risk applies to all AEDs used for any indication. The risk did not vary substantially by age (5-100 years) in the clinical trials analyzed. Table 2 shows absolute and relative risk by indication for all evaluated AEDs.

Table 2: Risk of Suicidal Thoughts or Behaviors by Indication for Antiepileptic Drugs in the Pooled Analysis
Indication | Placebo Patients with Events Per 1000 Patients | Drug Patients with Events Per 1000 Patients | Relative Risk: Incidence of Events in Drug Patients/Incidence in Placebo Patients | Risk Difference: Additional Drug Patients with Events Per 1000 Patients
Epilepsy | 1.0 | 3.4 | 3.5 | 2.4
Psychiatric | 5.7 | 8.5 | 1.5 | 2.9
Other | 1.0 | 1.8 | 1.9 | 0.9
Total | 2.4 | 4.3 | 1.8 | 1.9

The relative risk for suicidal thoughts or behavior was higher in clinical trials in patients with epilepsy than in clinical trials in patients with psychiatric or other conditions, but the absolute risk differences were similar for the epilepsy and psychiatric indications.

Anyone considering prescribing EPIDIOLEX or any other AED must balance the risk of suicidal thoughts or behaviors with the risk of untreated illness. Epilepsy and many other illnesses for which AEDs are prescribed are themselves associated with morbidity and mortality and an increased risk of suicidal thoughts and behavior. Should suicidal thoughts and behavior emerge during treatment, consider whether the emergence of these symptoms in any given patient may be related to the illness being treated.

5.4 Hypersensitivity Reactions

EPIDIOLEX can cause hypersensitivity reactions. Some subjects in the EPIDIOLEX clinical trials had pruritus, erythema, and angioedema requiring treatment, including corticosteroids and antihistamines. Patients with known or suspected hypersensitivity to any ingredients of EPIDIOLEX were excluded from the clinical trials. If a patient develops hypersensitivity reactions after treatment with EPIDIOLEX, the drug should be discontinued. EPIDIOLEX is contraindicated in patients with a prior hypersensitivity reaction to cannabidiol or any of the ingredients in the product, which includes sesame seed oil [see Description (11)].

5.5 Withdrawal of Antiepileptic Drugs (AEDs)

As with most antiepileptic drugs, EPIDIOLEX should generally be withdrawn gradually because of the risk of increased seizure frequency and status epilepticus [see Dosage and Administration (2.5) and Clinical Studies (14)]. But if withdrawal is needed because of a serious adverse event, rapid discontinuation can be considered.

6 ADVERSE REACTIONS

The following important adverse reactions are described elsewhere in labeling:

- Hepatic Injury [see Warnings and Precautions (5.1)]
- Somnolence and Sedation [see Warnings and Precautions (5.2)]
- Suicidal Behavior and Ideation [see Warnings and Precautions (5.3)]
- Hypersensitivity Reactions [see Warnings and Precautions (5.4)]
- Withdrawal of Antiepileptic Drugs [see Warnings and Precautions (5.5)]

6.1 Clinical Trials Experience

Because clinical trials are conducted under widely varying conditions, adverse reaction rates observed in the clinical trials of a drug cannot be directly compared to rates in the clinical trials of another drug and may not reflect the rates observed in practice.

In controlled and uncontrolled trials in patients with LGS and DS, 689 patients were treated with EPIDIOLEX, including 533 patients treated for more than 6 months, and 391 patients treated for more than 1 year. In controlled and uncontrolled trials in patients with TSC, 223 patients were treated with EPIDIOLEX, including 151 patients treated for more than 6 months, 88 patients treated for more than 1 year, and 15 patients treated for more than 2 years.

In an expanded access program and other compassionate use programs, 271 patients with DS, LGS, or TSC were treated with EPIDIOLEX, including 237 patients treated for more than 6 months, 204 patients treated for more than 1 year, and 140 patients treated for more than 2 years.

Patients with LGS or DS

In placebo-controlled trials of patients with LGS or DS (includes Studies 1, 2, 3, and a Phase 2 controlled study in DS), 323 patients received EPIDIOLEX [see Clinical Studies (14.1, 14.2)]. Adverse reactions are presented below; the duration of treatment in these trials was up to 14 weeks. Approximately 46% of patients were female, 83% were Caucasian, and the mean age was 14 years (range 2 to 48 years). All patients were taking other AEDs.

In controlled trials in LGS or DS, the rate of discontinuation as a result of any adverse reaction was 2.7% for patients taking EPIDIOLEX 10 mg/kg/day, 11.8% for patients taking EPIDIOLEX 20 mg/kg/day, and 1.3% for patients on placebo. The most frequent cause of discontinuations was transaminase elevation. Discontinuation for transaminase elevation occurred at an incidence of 1.3% in patients taking EPIDIOLEX 10 mg/kg/day, 5.9% in patients taking EPIDIOLEX 20 mg/kg/day, and 0.4% in patients on placebo. Somnolence, sedation, and lethargy led to discontinuation in 3% of patients taking EPIDIOLEX 20 mg/kg/day compared to 0% of patients taking EPIDIOLEX 10 mg/kg/day or on placebo.

The most common adverse reactions that occurred in EPIDIOLEX-treated patients with LGS or DS (incidence at least 10% and greater than placebo) were somnolence; decreased appetite; diarrhea; transaminase elevations; fatigue, malaise, and asthenia; rash; insomnia, sleep disorder, and poor quality sleep; and infections.

Table 3 lists the adverse reactions that were reported in at least 3% of EPIDIOLEX-treated patients, and at a rate greater than those on placebo, in the placebo-controlled trials in LGS and DS.

Table 3: Adverse Reactions in Patients Treated with EPIDIOLEX in Controlled Trials of LGS and DS (Studies 1, 2, and 3)
Adverse Reactions | EPIDIOLEX |  | Placebo
Adverse Reactions | 10 mg/kg/day | 20 mg/kg/day | Placebo
Adverse Reactions | N=75 % | N=238 % | N=227 %
Hepatic Disorders
Transaminases elevated | 8 | 16 | 3
Gastrointestinal Disorders
Decreased appetite | 16 | 22 | 5
Diarrhea | 9 | 20 | 9
Weight decreased | 3 | 5 | 1
Gastroenteritis | 0 | 4 | 1
Abdominal pain, discomfort | 3 | 3 | 1
Nervous System Disorders
Somnolence | 23 | 25 | 8
Fatigue, malaise, asthenia | 11 | 12 | 4
Lethargy | 4 | 8 | 2
Sedation | 3 | 6 | 1
Irritability, agitation | 9 | 5 | 2
Aggression, anger | 3 | 5 | <1
Insomnia, sleep disorder, poor quality sleep | 11 | 5 | 4
Drooling, salivary hypersecretion | 1 | 4 | <1
Gait disturbance | 3 | 2 | <1
Infections
Infection, all | 41 | 40 | 31
Infection, other | 25 | 21 | 24
Infection, viral | 7 | 11 | 6
Pneumonia | 8 | 5 | 1
Infection, fungal | 1 | 3 | 0
Other
Rash | 7 | 13 | 3
Hypoxia, respiratory failure | 3 | 3 | 1

Adverse reactions were similar across LGS and DS in pediatric and adult patients.

Patients with TSC

In a placebo-controlled trial of patients with TSC (Study 4), 148 patients received EPIDIOLEX [see Clinical Studies (14.3)]. Adverse reactions are presented below; the duration of treatment in this trial was up to 16 weeks. Approximately 42% of patients were female, 90% were Caucasian, and the mean age was 14 years (range 1 to 57 years). All patients but one (25 mg/kg/day group) were taking other AEDs.

In the controlled trial in TSC, the rate of discontinuation as a result of any adverse reaction was 11% for patients taking EPIDIOLEX 25 mg/kg/day and 3% for patients on placebo. The most frequent cause of discontinuation was rash (5%).

The most common adverse reactions that occurred in EPIDIOLEX-treated patients with TSC (incidence at least 10% at the recommended dosage and greater than placebo) were diarrhea; transaminase elevations; decreased appetite; somnolence; pyrexia; and vomiting.

Table 4 lists the adverse reactions that were reported in at least 3% of EPIDIOLEX-treated patients, and at a rate greater than those on placebo, in the placebo-controlled trial in TSC.

Table 4: Adverse Reactions in Patients Treated with EPIDIOLEX in Controlled Trial of TSC (Study 4)
Adverse Reactions | EPIDIOLEX | Placebo
 | 25 mg/kg/day
 | N = 75 % | N = 76 %
Hematological changes
Anemia | 7 | 1
Platelet count decreased | 5 | 1
Eosinophil count increased | 5 | 0
Hepatic Disorders
Transaminases elevated | 25 | 0
Gastrointestinal Disorders
Diarrhea | 31 | 25
Decreased appetite | 20 | 12
Vomiting | 17 | 9
Nausea | 9 | 3
Gastroenteritis | 8 | 7
Weight decreased | 7 | 0
Nervous System Disorders
Somnolence | 13 | 9
Gait disturbance | 9 | 5
Fatigue, malaise, asthenia | 5 | 1
Infections
Ear infection | 8 | 3
Urinary tract infection | 5 | 0
Pneumonia | 4 | 1
Other
Pyrexia | 19 | 8
Rash | 8 | 4
Rhinorrhea | 4 | 0

Adverse reactions were similar in pediatric and adult patients with TSC.

Additional Adverse Reactions in Patients with LGS, DS, or TSC

Decreased Weight

EPIDIOLEX can cause weight loss. In the controlled trials of patients with LGS or DS (10 and 20 mg/kg/day), based on measured weights, 16% of EPIDIOLEX-treated patients had a decrease in weight of at least 5% from their baseline weight, compared to 8% of patients on placebo. The decrease in weight appeared to be dose-related, with 18% of patients on EPIDIOLEX 20 mg/kg/day experiencing a decrease in weight at least 5%, compared to 9% in patients on EPIDIOLEX 10 mg/kg/day. In the controlled trial of patients with TSC (25 mg/kg/day), 31% of EPIDIOLEX-treated patients had a decrease in weight of at least 5% from their baseline weight, compared to 8% of patients on placebo. In some cases, the decreased weight was reported as an adverse event (see Tables 3 and 4).

Hematologic Abnormalities

EPIDIOLEX can cause decreases in hemoglobin and hematocrit. In controlled trials of patients with LGS or DS, the mean decrease in hemoglobin from baseline to end of treatment was -0.42 g/dL in EPIDIOLEX-treated patients receiving 10 or 20 mg/kg/day and -0.03 g/dL in patients on placebo. A corresponding decrease in hematocrit was also observed, with a mean change of -1.5% in EPIDIOLEX-treated patients, and -0.4% in patients on placebo. In the trial of patients with TSC, the mean decrease in hemoglobin from baseline to end of treatment was -0.37 g/dL in EPIDIOLEX-treated patients receiving 25 mg/kg/day and 0.07 g/dL in patients on placebo. A corresponding decrease in hematocrit was also observed, with a mean change of -1.2% in EPIDIOLEX-treated patients, and -0.2% in patients on placebo.

There was no effect on red blood cell indices. Thirty percent (30%) of EPIDIOLEX-treated patients with LGS and DS and 38% of EPIDIOLEX-treated patients with TSC developed a new laboratory-defined anemia during the course of the study (defined as a normal hemoglobin concentration at baseline, with a reported value less than the lower limit of normal at a subsequent time point), versus 13% of patients with LGS and DS on placebo and 15% of patients with TSC on placebo.

Increases in Creatinine

EPIDIOLEX can cause elevations in serum creatinine. The mechanism has not yet been determined. In controlled studies in healthy adults and in patients with LGS, DS, and TSC, an increase in serum creatinine of approximately 10% was observed within 2 weeks of starting EPIDIOLEX. The increase was reversible in healthy adults. Reversibility was not assessed in studies in LGS, DS, or TSC.

Increases in Pneumonia with Concomitant Clobazam

Pneumonia has been observed in controlled trials in patients with LGS and DS more frequently with clobazam (7 of 41 [17%] in patients receiving 10 mg/kg/day EPIDIOLEX, 13 of 125 [10%] in patients receiving 20 mg/kg/day EPIDIOLEX, and 1 of 123 [1%] receiving placebo) than without concomitant clobazam (0% in patients receiving 10 mg/kg/day EPIDIOLEX, 4 of 113 [4%] in patients receiving 20 mg/kg/day EPIDIOLEX, and 1 of 104 [1%] receiving placebo). In the controlled trial in patients with TSC, pneumonia was observed more frequently with concomitant clobazam (3 of 18 [17%] in patients receiving 25 mg/kg/day EPIDIOLEX and 0 of 25 [0%] receiving placebo) than without clobazam (0 of 57 [0%] in patients receiving 25 mg/kg/day EPIDIOLEX and 1 of 51 [2%] receiving placebo).

7 DRUG INTERACTIONS

7.1 Effect of Other Drugs on EPIDIOLEX

Strong CYP3A4 or CYP2C19 Inducers

Concomitant use with a strong CYP3A4 and CYP2C19 inducer (rifampin 600 mg once daily) decreased cannabidiol and 7‑OH‑CBD plasma concentrations by approximately 32% and 63%. The impact of such changes on efficacy of EPIDIOLEX is not known [see Clinical Pharmacology (12.3)]. Consider an increase in EPIDIOLEX dosage (based on clinical response and tolerability) up to 2‑fold, when concomitantly used with a strong CYP3A4 and/or CYP2C19 inducer.

7.2 Effect of EPIDIOLEX on Other Drugs

Antiepileptic Drugs

Clobazam

Concomitant use of EPIDIOLEX with clobazam increases plasma concentrations of N‑desmethylclobazam, the active metabolite of clobazam [see Clinical Pharmacology (12.3)], which may increase the risk of clobazam-related adverse reactions [see Adverse Reactions (6.1) and Warnings and Precautions (5.1, 5.2)]. Consider a reduction in dosage of clobazam if adverse reactions known to occur with clobazam are experienced when concomitantly used with EPIDIOLEX.

Stiripentol

Concomitant use of EPIDIOLEX with stiripentol increases plasma exposures of stiripentol [see Clinical Pharmacology (12.3)]. Monitor for stiripentol-related adverse reactions when concomitantly used with EPIDIOLEX.

Orally Administered P-gp Substrates

Concomitant use of EPIDIOLEX with orally administered everolimus results in an approximately 2.5‑fold increase in plasma exposures of everolimus [see Clinical Pharmacology (12.3)]. When initiating EPIDIOLEX in patients taking everolimus, monitor therapeutic drug levels of everolimus and adjust the dosage accordingly. In patients on a stable dosage of EPIDIOLEX, it is recommended to initiate everolimus at a lower starting dosage and titrate the dose based on therapeutic drug monitoring.

Increases in exposure of other orally administered P‑gp substrates (e.g., sirolimus, tacrolimus, digoxin) may be observed when concomitantly used with EPIDIOLEX. Consider therapeutic drug monitoring and dosage reduction of other P‑gp substrates when given orally with EPIDIOLEX.

CYP1A2, CYP2B6, CYP2C8, CYP2C19, and UGT1A9 Substrates

CYP1A2 Substrates

Cannabidiol is a weak inhibitor of CYP1A2 [see Clinical Pharmacology (12.3)]. Increases in exposure of certain CYP1A2 substrates (e.g., theophylline, tizanidine) may be observed when concomitantly used with EPIDIOLEX. Consider dosage reduction of CYP1A2 substrates where minimal concentration changes may lead to serious adverse reactions, as clinically appropriate, when concomitantly used with EPIDIOLEX.

CYP2B6 Substrates

Cannabidiol is an inducer and inhibitor of CYP2B6 [see Clinical Pharmacology (12.3)]. No clinically significant reduction in exposures of CYP2B6 substrates are observed when concomitantly used with EPIDIOLEX at 7.5 mg/kg twice daily. Changes in exposures of CYP2B6 substrates are unknown when concomitantly used with EPIDIOLEX at doses above 7.5 mg/kg twice daily. Consider dosage modification of CYP2B6 substrates, as clinically appropriate, when concomitantly used with EPIDIOLEX at doses above 7.5 mg/kg twice daily.

CYP2C8 Substrates

Concomitant use of EPIDIOLEX may cause clinically significant interactions with CYP2C8 substrates. Consider a reduction in dosage of CYP2C8 substrates, as clinically appropriate, if adverse reactions are experienced when concomitantly used with EPIDIOLEX.

CYP2C19 Substrates

Cannabidiol is a moderate inhibitor of CYP2C19 [see Clinical Pharmacology (12.3)]. Concomitant use of EPIDIOLEX increases plasma concentrations of CYP2C19 substrates and may increase the risk of adverse reactions. Consider a dosage reduction of CYP2C19 substrates, as clinically appropriate, when concomitantly used with EPIDIOLEX.

For CYP2C19 substrates (e.g., clopidogrel) where efficacy is mainly due to their active metabolite(s), concomitant use of EPIDIOLEX may decrease plasma concentration of the active metabolite(s) and may therefore decrease efficacy. Consider a dosage increase of such CYP2C19 substrates, as clinically appropriate, when concomitantly used with EPIDIOLEX.

UGT1A9 Substrates

Cannabidiol is an inhibitor of UGT1A9 [see Clinical Pharmacology (12.3)]. Increases in exposure of UGT1A9 substrates may be observed when concomitantly used with EPIDIOLEX. Consider a reduction in dosage of UGT1A9 substrates where minimal concentration changes may lead to serious adverse reactions, as clinically appropriate, when concomitantly used with EPIDIOLEX.

7.3 Concomitant Use of EPIDIOLEX and Valproate

Concomitant use of EPIDIOLEX and valproate increases the incidence of liver enzyme elevations [see Warnings and Precautions (5.1)]. If such elevations occur, consider discontinuation or reduction of EPIDIOLEX and/or concomitant valproate. Insufficient data are available to assess the risk of concomitant administration of other hepatotoxic drugs and EPIDIOLEX.

7.4 CNS Depressants and Alcohol

Concomitant use of EPIDIOLEX with other CNS depressants (including alcohol) may increase the risk of sedation and somnolence [see Warnings and Precautions (5.2)].

8 USE IN SPECIFIC POPULATIONS

8.1 Pregnancy

Pregnancy Surveillance Program and Pregnancy Exposure Registry

There are two programs, an EPIDIOLEX pregnancy surveillance program and an antiepileptic drug (AED) pregnancy exposure registry, that monitor pregnancy outcomes. Encourage women who are taking EPIDIOLEX during pregnancy to enroll in both, by calling the toll free numbers or visiting the websites below:

- EPIDIOLEX Pregnancy Surveillance Program
  - 1-855-272-7158
  - https://www.epidiolexpregnancystudy.com
- North American Antiepileptic Drug (NAAED) Pregnancy Registry
  - 1-888-233-2334
  - https://www.aedpregnancyregistry.org/

Risk Summary

There are no adequate data on the developmental risks associated with the use of EPIDIOLEX in pregnant women. Administration of cannabidiol to pregnant animals produced evidence of developmental toxicity (increased embryofetal mortality in rats and decreased fetal body weights in rabbits; decreased growth, delayed sexual maturation, long-term neurobehavioral changes, and adverse effects on the reproductive system in rat offspring) at maternal plasma exposures similar to (rabbit) or greater than (rat) that in humans at therapeutic doses (see Animal Data). In the U.S. general population, the estimated background risk of major birth defects and miscarriage in clinically recognized pregnancies is 2–4% and 15–20%, respectively. The background risks of major birth defects and miscarriage for the indicated populations are unknown.

Data

Animal Data

Oral administration of cannabidiol (0, 75, 150, or 250 mg/kg/day) to pregnant rats throughout the period of organogenesis resulted in embryofetal mortality at the highest dose tested. There were no other drug-related maternal or developmental effects. The highest no-effect dose for embryofetal toxicity in rats was associated with maternal plasma cannabidiol exposures (AUC) approximately 16 and 9 times that in humans at the recommended human doses (RHD) of 20 and 25 mg/kg/day, respectively.

Oral administration of cannabidiol (0, 50, 80, or 125 mg/kg/day) to pregnant rabbits throughout organogenesis resulted in decreased fetal body weights and increased fetal structural variations at the highest dose tested, which was also associated with maternal toxicity. Maternal plasma cannabidiol exposures at the no-effect level for embryofetal developmental toxicity in rabbits were less than that in humans at the RHDs.

When cannabidiol (75, 150, or 250 mg/kg/day) was orally administered to rats throughout pregnancy and lactation, decreased growth, delayed sexual maturation, neurobehavioral changes (decreased activity), and adverse effects on male reproductive organ development (small testes in adult offspring) and fertility were observed in the offspring at the mid and high dose. These effects occurred in the absence of maternal toxicity. The no-effect dose for pre- and post-natal developmental toxicity in rats was associated with maternal plasma cannabidiol exposures approximately 9 and 5 times that in humans at the RHDs of 20 and 25 mg/kg/day, respectively.

8.2 Lactation

Risk Summary

There are no data on the presence of cannabidiol or its metabolites in human milk, the effects on the breastfed infant, or the effects on milk production. The developmental and health benefits of breastfeeding should be considered along with the mother’s clinical need for EPIDIOLEX and any potential adverse effects on the breastfed infant from EPIDIOLEX or from the underlying maternal condition.

8.4 Pediatric Use

Safety and effectiveness of EPIDIOLEX for the treatment of seizures associated with LGS, DS, or TSC have been established in patients 1 year of age and older. The use of EPIDIOLEX in these indications is supported by adequate and well-controlled studies in patients 2 years of age and older with LGS and DS and in patients 1 year of age and older with TSC [see Clinical Studies (14.1, 14.2, 14.3)].

Safety and effectiveness of EPIDIOLEX in pediatric patients below 1 year of age have not been established.

Juvenile Animal Data

Administration of cannabidiol (subcutaneous doses of 0 or 15 mg/kg on Postnatal Days (PNDs) 4-6 followed by oral administration of 0, 100, 150, or 250 mg/kg on PNDs 7-77) to juvenile rats for 10 weeks resulted in increased body weight, delayed male sexual maturation, neurobehavioral effects (decreased locomotor activity and auditory startle habituation), increased bone mineral density, and liver hepatocyte vacuolation. A no-effect dose was not established. The lowest dose causing developmental toxicity in juvenile rats (15 sc/100 po mg/kg) was associated with cannabidiol exposures (AUC) approximately 15 and 8 times that in humans at the RHDs of 20 and 25 mg/kg/day, respectively.

8.5 Geriatric Use

Clinical trials of EPIDIOLEX in the treatment of LGS, DS, and TSC did not include a sufficient number of patients aged above 55 years to determine whether or not they respond differently from younger patients. In general, dose selection for an elderly patient should be cautious, usually starting at the low end of the dosing range, reflecting the greater frequency of decreased hepatic, renal, or cardiac function, and of concomitant disease or other drug therapy [see Dosage and Administration (2.6), Warnings and Precautions (5.1), and Clinical Pharmacology (12.3)].

8.6 Hepatic Impairment

Because of an increase in exposure to EPIDIOLEX, dosage adjustments are necessary in patients with moderate or severe hepatic impairment [see Dosage and Administration (2.6), Warnings and Precautions (5.1), and Clinical Pharmacology (12.3)]. EPIDIOLEX does not require dosage adjustments in patients with mild hepatic impairment.

9 DRUG ABUSE AND DEPENDENCE

9.1 Controlled Substance

EPIDIOLEX is not a controlled substance.

9.2 Abuse

Animal abuse-related studies show that cannabidiol does not produce cannabinoid-like behavioral responses, including generalization to delta-9-tetrahydrocannabinol (THC) in a drug discrimination study. Cannabidiol also does not produce animal self-administration, suggesting it does not produce rewarding effects. In a human abuse potential study, acute administration of cannabidiol to non-dependent adult recreational drug users at therapeutic and supratherapeutic doses of 750, 1500, and 4500 mg in the fasted state (equivalent respectively to 10, 20, and 60 mg/kg in a 75 kg adult) produced responses on positive subjective measures such as Drug Liking and Take Drug Again that were within the acceptable placebo range. In contrast, 10 and 30 mg of dronabinol (synthetic THC) and 2 mg alprazolam produced large increases on positive subjective measures compared to placebo that were statistically significantly greater than those produced by cannabidiol. In other Phase 1 clinical studies conducted with cannabidiol, there were no reports of abuse-related adverse events.

9.3 Dependence

In a human physical dependence study, administration of cannabidiol 1500 mg/day (750 mg twice daily) to adults for 28 days did not produce signs or symptoms of withdrawal over a 6-week assessment period beginning three days after drug discontinuation. This suggests that cannabidiol likely does not produce physical dependence.

11 DESCRIPTION

Cannabidiol is a cannabinoid designated chemically as 2-[(1R,6R)-3-Methyl-6-(1-methylethenyl)-2-cyclohexen-1-yl]-5-pentyl-1,3-benzenediol (IUPAC/CAS). Its empirical formula is C21H30O2 and its molecular weight is 314.46. The chemical structure is:

Cannabidiol, the active ingredient in EPIDIOLEX, is a cannabinoid that naturally occurs in the Cannabis sativa L. plant.

Cannabidiol is a white to pale yellow crystalline solid. It is insoluble in water and is soluble in organic solvents.

EPIDIOLEX (cannabidiol) oral solution is a clear, colorless to yellow liquid containing cannabidiol at a concentration of 100 mg/mL. Inactive ingredients include dehydrated alcohol (7.9% w/v), sesame seed oil, strawberry flavor, and sucralose. EPIDIOLEX contains no ingredient made from a gluten-containing grain (wheat, barley, or rye).

12 CLINICAL PHARMACOLOGY

12.1 Mechanism of Action

The precise mechanisms by which EPIDIOLEX exerts its anticonvulsant effect in humans are unknown. Cannabidiol does not appear to exert its anticonvulsant effects through interaction with cannabinoid receptors.

12.2 Pharmacodynamics

Cardiac Electrophysiology

Concentration-dependent QTc prolongation was observed for EPIDIOLEX. At exposures obtained when administered as monotherapy at recommended doses with a high fat meal, EPIDIOLEX did not prolong the QTc interval greater than 10 msec.

Other factors such as food intake, certain concomitant medications (e.g., clobazam), and alcohol consumption may increase the exposure of EPIDIOLEX and the potential effect on QTc prolongation in this scenario is not known.

12.3 Pharmacokinetics

Cannabidiol demonstrated an increase in exposure that was less than dose-proportional over the range of 5 to 25 mg/kg/day in patients.

Absorption

Cannabidiol has a time to maximum plasma concentration (Tmax) of 2.5 to 5 hours at steady state (Css).

Effect of Food

Coadministration of EPIDIOLEX (750 or 1500 mg) with a high-fat/high-calorie meal increased Cmax by 5‑fold, AUC by 4‑fold, and reduced the total variability, compared with the fasted state in healthy subjects [see Dosage and Administration (2.4)]. Coadministration of EPIDIOLEX with a low-fat/low-calorie meal increased Cmax and AUC by 4‑fold and 3‑fold, respectively. Furthermore, coadministration of EPIDIOLEX with bovine milk increased exposure by approximately 3‑fold for Cmax and 2.5‑fold for AUC. Coadministration of EPIDIOLEX with alcohol also caused increased exposure to cannabidiol, with 93% increased Cmax and 63% greater AUC.

Distribution

The apparent volume of distribution in healthy subjects was 20963 L to 42849 L. Protein binding of the cannabidiol and its metabolites was > 94% in vitro.

Elimination

The half-life of cannabidiol in plasma was 56 to 61 hours after twice-daily dosing for 7 days in healthy subjects. The plasma clearance of cannabidiol following a single EPIDIOLEX 1500 mg dose (approximately equal to the 20 mg/kg/day dosage) is 1111 L/h.

Metabolism

Cannabidiol is metabolized in the liver and the gut (primarily in the liver) by CYP2C19 and CYP3A4 enzymes, and UGT1A7, UGT1A9, and UGT2B7 isoforms.

After repeat dosing, the active metabolite of cannabidiol, 7‑OH-CBD, has a 38% lower AUC than the parent drug. The 7‑OH-CBD metabolite is converted to 7‑COOH‑CBD, which has an approximately 40‑fold higher AUC than the parent drug. Based on preclinical models of seizure, the 7‑OH‑CBD metabolite is active; however, the 7‑COOH‑CBD metabolite is not active.

Excretion

EPIDIOLEX is excreted in feces, with minor renal clearance.

Specific Populations

Patients with Hepatic Impairment

No effects on the exposures of cannabidiol or metabolite exposures were observed following administration of a single dose of EPIDIOLEX 200 mg in patients with mild (Child-Pugh A) hepatic impairment. Patients with moderate (Child-Pugh B) or severe (Child-Pugh C) hepatic impairment had an approximately 2.5 to 5.2-fold higher AUC, compared with healthy subjects with normal hepatic function [see Dosage and Administration (2.6), Warnings and Precautions (5.1), and Use in Specific Populations (8.6)].

Drug Interaction Studies

Clinical Studies and Model-Informed Approaches

Drug Interaction Studies with AEDs

Clobazam and Valproate

The interaction potential with other AEDs (clobazam and valproate) was evaluated in dedicated clinical studies following coadministration of EPIDIOLEX (750 mg twice daily in healthy subjects and 20 mg/kg/day in patients).

Coadministration with clobazam in healthy subjects increased the cannabidiol active metabolite 7‑OH‑CBD mean Cmax by 73% and AUC by 47%; and increased the clobazam active metabolite, N‑desmethylclobazam, a substrate of CYP2C19, Cmax and AUC by approximately 3‑fold, with no effect on clobazam levels [see Drug Interactions (7.2)].

When EPIDIOLEX was coadministered with valproate in healthy subjects, there was no effect on the systemic exposure to valproate. In a separate study in epilepsy patients investigating the effect of EPIDIOLEX on valproate exposure, there were decreases in both the plasma Cmax and AUC of valproate, which were not clinically relevant (approximately 17% and 21%, respectively), and a decrease in exposure of the putative hepatotoxic metabolite of valproate, 2‑propyl‑4‑pentanoic acid (approximately 28% and 33%, respectively).

In healthy subjects, coadministration with valproate resulted in no clinically relevant changes in exposure to cannabidiol or its major metabolites (cannabidiol Cmax decreased by 26%; 6‑OH‑CBD AUC increased by 27%; 7‑OH‑CBD AUC increased by 22%; 7‑COOH‑CBD Cmax and AUC increased by 25% and 32%, respectively).

Stiripentol

When EPIDIOLEX was coadministered with stiripentol in healthy subjects, Cmax and AUC of stiripentol increased 28% and 55%, respectively. In patients with epilepsy, Cmax and AUC of stiripentol increased 17% and 30%, respectively [see Drug Interactions (7.2)].

Everolimus

Coadministration of EPIDIOLEX (12.5 mg/kg twice daily) with the P-gp and CYP3A4 substrate everolimus (5 mg) in healthy subjects led to an approximately 2.5-fold increase in everolimus mean Cmax and AUC [see Drug Interactions (7.2)].

Effect of Other Drugs on EPIDIOLEX

CYP3A4 and CYP2C19 Inhibitors

Coadministration of EPIDIOLEX with strong inhibitors of CYP3A4 or CYP2C19 had the following effects on exposure to cannabidiol and its metabolites. Itraconazole, a strong CYP3A4 inhibitor, increased exposure by < 10% for cannabidiol and < 20% for 7-OH-CBD and 7-COOH-CBD for both AUC and Cmax. Although the effects of a strong CYP2C19 inhibitor fluconazole were slightly more marked, they are still considered not to be clinically meaningful (cannabidiol increased by 22% and 24% for AUC and Cmax, respectively; 7‑OH‑CBD decreased by 28% and 41% for AUC and Cmax; 7‑COOH‑CBD decreased by 33% and 48% for AUC and Cmax).

CYP3A4 and CYP2C19 Inducers

Coadministration with rifampin, a strong CYP3A4 and CYP2C19 inducer, caused a decrease in cannabidiol exposure of 32% and 34% for AUC and Cmax [see Drug Interactions (7.1)]. There were larger changes in exposure to the active metabolite (7-OH-CBD decreased by 63% and 67% for AUC and Cmax, 7‑COOH‑CBD decreased by 48% for AUC, whereas there was no change in Cmax).

Effect of EPIDIOLEX on Other Drugs

CYP1A2 Substrates

Coadministration of EPIDIOLEX (750 mg twice daily) with a single dose of caffeine (200 mg), a sensitive CYP1A2 substrate, showed increased caffeine exposure by 15% for Cmax and 95% for AUC compared to caffeine administered alone [see Drug Interactions (7.2)].

CYP2B6 Substrates

Coadministration of EPIDIOLEX (7.5 mg/kg twice daily) with a single dose of bupropion (150 mg), a CYP2B6 substrate, decreased bupropion exposure by 19% for Cmax and 20% for AUC compared to bupropion administered alone. The Cmax and AUC of hydroxybupropion, an active metabolite formed by CYP2B6, was not altered. The effect of EPIDIOLEX doses above 7.5 mg/kg twice daily on bupropion and hydroxybupropion is unknown [see Drug Interactions (7.2)].

CYP2C9 Substrates

Coadministration of EPIDIOLEX (7.5 mg/kg twice daily) with a single dose of tolbutamide (500 mg), a moderately sensitive CYP2C9 substrate, did not result in changes in plasma exposures of tolbutamide compared to tolbutamide administered alone. No clinically meaningful changes in plasma exposures of tolbutamide were predicted when tolbutamide is coadministered with steady-state dosing of EPIDIOLEX (12.5 mg/kg twice daily).

CYP3A4 Substrates

Coadministration of EPIDIOLEX (750 mg twice daily) with a single dose of midazolam (2.5 mg), a sensitive CYP3A4 substrate, did not result in changes in plasma concentrations of midazolam compared to midazolam administered alone.

UGT1A9 Substrates

Coadministration of EPIDIOLEX (7.5 mg/kg twice daily) with a single dose of mycophenolate mofetil (1500 mg), a UGT1A9 substrate, increased mycophenolic acid exposure by 16% for Cmax and 35% for AUC when compared to mycophenolate mofetil administered alone. An increase in mycophenolic acid exposure by 9% for Cmax and 58% for AUC is predicted when mycophenolate mofetil (1500 mg) is coadministered with steady-state dosing of EPIDIOLEX (12.5 mg/kg twice daily) [see Drug Interactions (7.2)].

UGT2B7 Substrates

Coadministration of EPIDIOLEX (7.5 mg/kg twice daily) with a single dose of zidovudine (300 mg), a UGT2B7 substrate, increased zidovudine exposure by 7% for Cmax and 19% for AUC compared to zidovudine administered alone, which is not expected to be clinically significant. No clinically meaningful changes in plasma exposures of zidovudine are predicted when zidovudine is coadministered with steady-state dosing of EPIDIOLEX (12.5 mg/kg twice daily).

In Vitro Assessment of Drug Interactions

Drug Metabolizing Enzymes [see Drug Interactions (7.1, 7.2)]

Cannabidiol has the potential to inhibit CYP2B6 and CYP2C8, and to induce CYP2B6 at clinically relevant concentrations.

Cannabidiol does not inhibit the uridine 5'-diphospho-glucuronosyltransferase (UGT) enzymes UGT1A1, UGT1A3, UGT1A4, UGT1A6, or UGT2B17 isoforms.

Transporters

Cannabidiol and the cannabidiol metabolite, 7-OH-CBD, are not anticipated to interact with BCRP, BSEP, MDR1/P‑gp, OAT1, OAT3, OCT1, OCT2, MATE1, MATE2‑K, OATP1B1, or OATP1B3. However, due to limitations of the in vitro testing procedure, inhibition of P‑gp mediated efflux by cannabidiol in the intestine could not be excluded. In vivo data show that CBD can affect P‑gp efflux activity in the intestine [see Clinical Studies and Model-Informed Approaches].

The cannabidiol metabolite, 7‑COOH‑CBD, is not a substrate of BCRP, OATP1B1, OATP1B3, or OCT1. However, 7‑COOH‑CBD is a substrate for P‑gp. 7‑COOH‑CBD is an inhibitor of transport mediated via BCRP and BSEP at clinically relevant concentrations.

13 NONCLINICAL TOXICOLOGY

13.1 Carcinogenesis and Mutagenesis

Carcinogenesis

In a carcinogenicity study in mice, oral administration of cannabidiol (0 [water], 0 [vehicle], 30, 100, or 300 mg/kg/day) for 2 years resulted in an increased incidence of hepatocellular adenomas in male mice at the highest dose tested. At the mid dose (100 mg/kg/day), plasma exposures (AUC) were approximately 5 and 3 times that at the recommended human doses (RHDs) of 20 and 25 mg/kg/day, respectively.

The carcinogenic potential of cannabidiol has not been assessed in rats.

Mutagenesis

Cannabidiol was negative for genotoxicity in in vitro (Ames) and in vivo (rat Comet and bone marrow micronucleus) assays.

Impairment of Fertility

Oral administration of cannabidiol (0, 75, 150, or 250 mg/kg/day) to male and female rats, prior to and throughout mating and continuing in females during early gestation, produced no adverse effects on fertility. The highest dose tested was associated with plasma exposures (AUC) approximately 60 and 34 times that in humans at the RHDs of 20 and 25 mg/kg/day, respectively.

14 CLINICAL STUDIES

14.1 Lennox–Gastaut Syndrome

The effectiveness of EPIDIOLEX for the treatment of seizures associated with LGS was established in two randomized, double-blind, placebo-controlled trials in patients aged 2 to 55 years (Study 1, NCT02224690; and Study 2, NCT02224560).

Study 1 (N=171) compared a dose of EPIDIOLEX 20 mg/kg/day with placebo. Study 2 (N=225) compared a 10 mg/kg/day dose and a 20 mg/kg/day dose of EPIDIOLEX with placebo. In both studies, patients had a diagnosis of LGS and were inadequately controlled on at least one AED, with or without vagal nerve stimulation and/or ketogenic diet. Both trials had a 4-week baseline period, during which patients were required to have a minimum of 8 drop seizures (≥ 2 drop seizures per week). The baseline period was followed by a 2-week titration period and a 12-week maintenance period.

In Study 1, 94% of patients were taking at least 2 concomitant AEDs. The most frequently used concomitant AEDs (greater than 25%) in Study 1 were clobazam (49%), valproate (40%), lamotrigine (37%), levetiracetam (34%), and rufinamide (27%). In Study 2, 94% of patients were taking at least 2 concomitant AEDs. The most frequently used concomitant AEDs (greater than 25%) in Study 2, were clobazam (49%), valproate (38%), levetiracetam (31%), lamotrigine (30%), and rufinamide (29%).

The primary efficacy measure in both studies was the percent change from baseline in the frequency (per 28 days) of drop seizures (atonic, tonic, or tonic-clonic seizures) over the 14-week treatment period. Key secondary endpoints in both studies included analyses of change in total seizure frequency and changes from baseline in the Subject/Caregiver Global Impression of Change (S/CGIC) score at the last visit. For the S/CGIC, the following question was rated on a 7-point scale: “Since [you/your child] started treatment, please assess the status of [your/your child’s] overall condition (comparing [your/their] condition now to [your/their] condition before treatment) using the scale below.” The 7-point scale was as follows: “Very Much Improved” (1); “Much Improved” (2); “Slightly Improved” (3); “No Change” (4); “Slightly Worse” (5); “Much Worse” (6); “Very Much Worse” (7).

In Studies 1 and 2, the median percent change from baseline (reduction) in the frequency of drop seizures was significantly greater for both dosage groups of EPIDIOLEX than for placebo (Table 5). A reduction in drop seizures was observed within 4 weeks of initiating treatment with EPIDIOLEX, and the effect remained generally consistent over the 14-week treatment period.

Table 5: Change in Drop Seizure Frequency in Lennox–Gastaut Syndrome during the Treatment Period (Studies 1 and 2)
Drop Seizure Frequency (per 28 Days) | Placebo | EPIDIOLEX 10 mg/kg/day | EPIDIOLEX 20 mg/kg/day
Study 1 | N=85 | — | N=86
Baseline Period Median Seizure Frequency | 75 | — | 71
Median Percentage Change from Baseline During Treatment | −22 | — | −44
p-value compared to placeboa |  |  | 0.01
Study 2 | N=76 | N=73 | N=76
Baseline Period Median Seizure Frequency | 80 | 87 | 86
Median Percentage Change from Baseline During Treatment | −17 | −37 | −42
p-value compared to placeboa |  | <0.01 | <0.01

aObtained from a Wilcoxon rank-sum test.

Figure 1 displays the percentage of patients by category of reduction from baseline in drop seizure frequency per 28 days during the treatment period in Study 1.

Figure 1: Proportion of Patients by Category of Seizure Response for EPIDIOLEX and Placebo in Patients with Lennox–Gastaut Syndrome (Study 1)

Figure 2 displays the percentage of patients by category of reduction from baseline in drop seizure frequency (per 28 days) during the treatment period in Study 2.

Figure 2: Proportion of Patients by Category of Seizure Response for EPIDIOLEX and Placebo in Patients with Lennox–Gastaut Syndrome (Study 2)

In Study 1, 3 of 85 (4%) patients in the EPIDIOLEX 20 mg/kg/day group reported no drop seizures during the maintenance period, compared to 0 patients in the placebo group. In Study 2, 3 of 73 (4%) patients in the EPIDIOLEX 10 mg/kg/day group, 5 of 76 (7%) patients in the EPIDIOLEX 20 mg/kg/day group, and 1 of 76 (1%) patients in the placebo group reported no drop seizures during the maintenance period.

In LGS patients, EPIDIOLEX was associated with significant reductions in total seizure frequency (drop and non-drop seizures) versus placebo. During the treatment period in Study 1, the median percent reduction in total seizure frequency (per 28 days) was 41% in patients taking EPIDIOLEX 20 mg/kg/day compared to 14% in patients taking placebo (p<0.01). In Study 2, the median percent reduction in total seizure frequency (per 28 days) was 36% in the 10 mg/kg/day group, 38% in the 20 mg/kg/day group, and 18% in the placebo group (p<0.01 for both groups).

A greater improvement on the Subject/Caregiver Global Impression of Change (S/CGIC) was reported in patients treated with EPIDIOLEX compared with placebo in Studies 1 and 2. In Study 1, the mean S/CGIC score at last visit was 3.0 in the 20 mg/kg/day EPIDIOLEX group (corresponding to “slightly improved”) compared with 3.7 (most closely associated with “no change”) in the placebo group (p<0.01). In Study 2, the mean S/CGIC score at last visit was 3.0 and 3.2 in the 10 mg/kg/day and 20 mg/kg/day EPIDIOLEX groups, respectively (“slightly improved”), compared with 3.6 (“no change”) in the placebo group (p<0.01 and p=0.04, respectively).

14.2 Dravet Syndrome

The effectiveness of EPIDIOLEX for the treatment of seizures associated with DS was demonstrated in a single randomized, double-blind, placebo-controlled trial in 120 patients aged 2 to 18 years (Study 3, NCT02091375). Study 3 compared a dose of EPIDIOLEX 20 mg/kg/day with placebo. Patients had a diagnosis of treatment-resistant DS and were inadequately controlled with at least one concomitant AED, with or without vagal nerve stimulation or ketogenic diet. During the 4-week baseline period, patients were required to have at least 4 convulsive seizures while on stable AED therapy. The baseline period was followed by a 2-week titration period and a 12-week maintenance period. The primary efficacy measure was the percent change from baseline in the frequency (per 28 days) of convulsive seizures (all countable atonic, tonic, clonic, and tonic-clonic seizures) over the 14-week treatment period.

In Study 3, 93% of patients were taking at least 2 concomitant AEDs during the trial. The most commonly used concomitant AEDs (greater than 25%) in Study 3 were clobazam (65%), valproate (57%), stiripentol (43%), levetiracetam (28%), and topiramate (26%).

The median percent change from baseline (reduction) in the frequency of convulsive seizures was significantly greater for EPIDIOLEX 20 mg/kg/day than for placebo (Table 6). A reduction in convulsive seizures was observed within 4 weeks of initiating treatment with EPIDIOLEX and the effect remained generally consistent over the 14-week treatment period.

Table 6: Change in Convulsive Seizure Frequency in Dravet Syndrome during the Treatment Period (Study 3)
Total Convulsive Seizures (per 28 Days) | Placebo | EPIDIOLEX 20 mg/kg/day
Study 3 | N=59 | N=61
Baseline Period Median Seizure Frequency | 15 | 12
Median Percentage Change from Baseline During Treatment | −13 | −39
p-value compared to placeboa |  | 0.01

aObtained from a Wilcoxon rank-sum test.

Figure 3 displays the percentage of patients by category of reduction from baseline in convulsive seizure frequency (per 28 days) during the treatment period in Study 3.

Figure 3: Proportion of Patients by Category of Seizure Response for EPIDIOLEX and Placebo in Patients with Dravet Syndrome (Study 3)

In Study 3, 4 of 60 (7%) patients treated with EPIDIOLEX 20 mg/kg/day reported no convulsive seizures during the maintenance period, compared to 0 patients in the placebo group.

14.3 Tuberous Sclerosis Complex

The effectiveness of EPIDIOLEX for the treatment of seizures associated with TSC was demonstrated in a randomized, double-blind, placebo-controlled trial in 224 patients aged 1 to 65 years (Study 4; NCT02544763).

Study 4 (N=224) compared doses of EPIDIOLEX 25 mg/kg/day and 50 mg/kg/day (2 times the recommended maintenance dosage) with placebo. Patients had a diagnosis of TSC and seizures inadequately controlled with at least one concomitant AED, with or without vagal nerve stimulation or ketogenic diet. During the 4-week baseline period, patients had at least 8 seizures, with at least 1 seizure occurring in at least 3 of the 4 weeks (focal motor seizures without impairment of consciousness or awareness; focal seizures with impairment of consciousness or awareness; focal seizures evolving to bilateral generalized convulsive seizures and generalized seizures [tonic–clonic, tonic, clonic or atonic seizures]). The baseline period was followed by a 4-week titration period and a 12‑week maintenance period.

In Study 4, all patients but 1 (in EPIDIOLEX 25 mg/kg/day group) were taking 1-5 concomitant AEDs during the trial. The most commonly used concomitant AEDs (greater than 25%) were valproate (45%), vigabatrin (33%), levetiracetam (29%), and clobazam (27%). The baseline median TSC-associated seizure frequency was 57 per 28 days for the combined groups. The primary efficacy measure was the change in seizure frequency of TSC-associated seizures over the 16-week treatment period compared with baseline.

In Study 4, the percentage change from baseline (reduction) in the frequency of TSC-associated seizures was significantly greater for patients treated with EPIDIOLEX than for placebo (Table 7). A reduction in TSC-associated seizures was observed within 4 weeks of initiating treatment with EPIDIOLEX and the effect remained generally consistent over the 12-week maintenance period.

Table 7: Change in TSC-Associated Seizure Frequency during the Treatment Period (Study 4)
Total TSC-Associated Seizures (per 28 Days) | Placebo | EPIDIOLEX 25 mg/kg/day
Study 4 | N=76 | N=75
Baseline Period Median Seizure Frequency | 54 | 56
Median Percentage Change from Baseline During Treatment | −20 | −43
p-value compared to placeboa |  | <0.01
Percentage Change from Baseline During Treatment in Estimated Mean Seizure Frequencyb | −24 | −48
p-value compared to placebob |  | <0.01

aObtained from a Wilcoxon rank-sum test.
bObtained from a log-transformed ANCOVA.

Figure 4 displays the percentage of patients by category of reduction from baseline in TSC-associated seizure frequency (per 28 days) during the treatment period in Study 4.

Figure 4: Proportion of Patients by Category of Seizure Response for EPIDIOLEX and Placebo in Patients with Tuberous Sclerosis Complex (Study 4)

In Study 4, 4 of 71 (6%) patients treated with EPIDIOLEX 25 mg/kg/day reported no TSC-associated seizures during the maintenance period, compared to 0 patients in the placebo group.

16 HOW SUPPLIED/STORAGE AND HANDLING

16.1 How Supplied

EPIDIOLEX is a strawberry-flavored, clear, colorless to yellow solution supplied in an amber glass bottle with a child-resistant closure. EPIDIOLEX is available in bottles containing 60 mL (NDC 70127-100-06) or 100 mL of oral solution (NDC 70127-100-01). Each mL contains 100 mg of cannabidiol. EPIDIOLEX is packaged in a carton with two 1 mL calibrated oral dosing syringes, two 5 mL calibrated oral dosing syringes, and bottle adapters (NDC 70127-100-60 or NDC 70127‑100‑10).

16.2 Storage and Handling

Store EPIDIOLEX in an upright position at 20°C to 25°C (68°F to 77°F); excursions are permitted between 15°C to 30°C (59°F to 86°F) [see USP Controlled Room Temperature]. Do not freeze. Keep the cap tightly closed. Use within 12 weeks of first opening the bottle, then discard any remainder.

17 PATIENT COUNSELING INFORMATION

Advise the caregiver or patient to read the FDA-approved patient labeling (Medication Guide and Instructions for Use).

Administration Information

Advise patients who are prescribed EPIDIOLEX to use the adapter and oral dosing syringes provided [see Dosage and Administration (2.4) and Instructions for Use]. Provide instructions regarding which syringe to use and how to administer the specified dose, since EPIDIOLEX is supplied with 1 mL and 5 mL oral dispensing syringes.

Instruct patients to discard any unused EPIDIOLEX oral solution after 12 weeks of first opening the bottle [see Dosage and Administration (2.4)].

Hepatic Injury

Inform patients about the potential for elevations of liver enzymes. Discuss with the patient the importance of measuring hepatic laboratory values and having them evaluated by the healthcare provider before treatment with EPIDIOLEX and periodically during treatment [see Warnings and Precautions (5.1)]. Advise patients of the clinical signs or symptoms suggestive of hepatic dysfunction (e.g., unexplained nausea, vomiting, right upper quadrant abdominal pain, fatigue, anorexia, or jaundice and/or dark urine) and to contact a healthcare provider promptly if these signs or symptoms occur.

Somnolence and Sedation

Caution patients about operating hazardous machinery, including motor vehicles, until they are reasonably certain that EPIDIOLEX does not affect them adversely (e.g., impair judgment, thinking or motor skills) [see Warnings and Precautions (5.2)].

Suicidal Thinking and Behavior

Counsel patients, their caregivers, and their families that antiepileptic drugs, including EPIDIOLEX, may increase the risk of suicidal thoughts and behavior and advise them to be alert for the emergence or worsening of symptoms of depression, any unusual changes in mood or behavior, or the emergence of suicidal thoughts, behavior, or thoughts of self-harm. Instruct patients, caregivers, and families to report behaviors of concern immediately to healthcare providers [see Warnings and Precautions (5.3)].

Withdrawal of Antiepileptic Drugs (AEDs)

Advise patients not to discontinue use of EPIDIOLEX without consulting with their healthcare provider. EPIDIOLEX should normally be gradually withdrawn to reduce the potential for increased seizure frequency and status epilepticus [see Dosage and Administration (2.5) and Warnings and Precautions (5.5)].

Pregnancy Surveillance Program and Pregnancy Exposure Registry

Advise patients to notify their healthcare provider if they become pregnant or intend to become pregnant during EPIDIOLEX therapy. Encourage women who are taking EPIDIOLEX to enroll in both the EPIDIOLEX Pregnancy Surveillance Program and the North American Antiepileptic Drug (NAAED) Pregnancy Registry if they become pregnant. The surveillance program and exposure registry are collecting information about the safety of EPIDIOLEX and other antiepileptic drugs during pregnancy [see Use in Specific Populations (8.1)].

Drug Testing

Advise patients of the potential for positive cannabis drug screens.

Distributed by:
Jazz Pharmaceuticals, Inc.
Palo Alto, CA 94306

EPIDIOLEX® is a registered trademark of Jazz Pharmaceuticals plc or its subsidiaries.
© 2025 Jazz Pharmaceuticals, Inc.

MEDICATION GUIDE
EPIDIOLEX® (EH-peh-DYE-oh-lex)
(cannabidiol)
oral solution

Read this Medication Guide before you start taking EPIDIOLEX and each time you get a refill. There may be new information. This information does not take the place of talking to your healthcare provider about your medical condition or treatment.

What is the most important information I should know about EPIDIOLEX?

EPIDIOLEX can cause serious side effects, including:

1. EPIDIOLEX may cause liver problems. Your healthcare provider may order blood tests to check your liver before you start taking EPIDIOLEX and during treatment. In some cases, EPIDIOLEX treatment may need to be stopped. Call your healthcare provider right away if you develop any of these signs and symptoms of liver problems during treatment with EPIDIOLEX:

• loss of appetite, nausea, vomiting

• fever, feeling unwell, unusual tiredness

• yellowing of the skin or the whites of the eyes (jaundice)

• itching

• unusual darkening of the urine

• right upper stomach area pain or discomfort

2. EPIDIOLEX may cause you to feel sleepy, which may get better over time. Using certain medicines with EPIDIOLEX such as clobazam or alcohol may increase sleepiness. Do not drive, operate heavy machinery, or do other dangerous activities until you know how EPIDIOLEX affects you.
3. Like other antiepileptic drugs, EPIDIOLEX may cause suicidal thoughts or actions in a very small number of people, about 1 in 500.
  Call a healthcare provider right away if you have any of these symptoms, especially if they are new, worse, or worry you:

• thoughts about suicide or dying

• attempt to commit suicide

• new or worse depression

• new or worse anxiety

• feeling agitated or restless

• panic attacks

• trouble sleeping (insomnia)

• new or worse irritability

• acting aggressive, being angry, or violent

• acting on dangerous impulses

• an extreme increase in activity and talking (mania)

• other unusual changes in behavior or mood

How can I watch for early symptoms of suicidal thoughts and actions?

• Pay attention to any changes, especially sudden changes in mood, behaviors, thoughts, or feelings.

• Keep all follow-up visits with your healthcare provider as scheduled.

4. Do not stop taking EPIDIOLEX without first talking to your healthcare provider. Stopping a seizure medicine such as EPIDIOLEX suddenly can cause you to have seizures more often or seizures that do not stop (status epilepticus).

Call your healthcare provider between visits as needed, especially if you are worried about symptoms.

What is EPIDIOLEX?

- EPIDIOLEX is a prescription medicine that is used to treat seizures associated with Lennox-Gastaut syndrome, Dravet syndrome, or tuberous sclerosis complex in people 1 year of age and older.
- It is not known if EPIDIOLEX is safe and effective in children under 1 year of age.

Who should not take EPIDIOLEX?

Do not take EPIDIOLEX if you are allergic to cannabidiol or any of the ingredients in EPIDIOLEX. See the end of this Medication Guide for a complete list of ingredients in EPIDIOLEX.

Before taking EPIDIOLEX, tell your healthcare provider about all of your medical conditions, including if you:

- have or have had depression, mood problems or suicidal thoughts or behavior.
- have liver problems.
- have abused or been dependent on prescription medicines, street drugs or alcohol.
- are pregnant or plan to become pregnant. Tell your healthcare provider right away if you become pregnant while taking EPIDIOLEX. You and your healthcare provider will decide if you should take EPIDIOLEX while you are pregnant. If you become pregnant while taking EPIDIOLEX, talk to your healthcare provider about registering for both the EPIDIOLEX Pregnancy Surveillance Program and the North American Antiepileptic Drug (NAAED) registry. The purpose of the surveillance program and exposure registry is to collect information about the safety of EPIDIOLEX and other antiepileptic drugs during pregnancy.
  - You can enroll in the EPIDIOLEX Pregnancy Surveillance Program by calling the toll free number 1-855-272-7158 or visiting https://www.epidiolexpregnancystudy.com.
  - You can enroll in the North American Antiepileptic Drug Pregnancy Registry by calling the toll free number 1-888-233-2334 or visiting http://www.aedpregnancyregistry.org.
- are breastfeeding or plan to breastfeed. It is not known if EPIDIOLEX passes into your breast milk. Talk to your healthcare provider about the best way to feed your baby while taking EPIDIOLEX.

Tell your healthcare provider about all the medicines you take, including prescription and over-the-counter medicines, vitamins, herbal supplements, and any cannabis-based products.

EPIDIOLEX may affect the way other medicines work, and other medicines may affect how EPIDIOLEX works. Do not start or stop taking other medicines without talking to your healthcare provider. Know the medicines you take. Keep a list of them to show your healthcare provider and pharmacist when you get a new medicine.

Tell your healthcare provider if you are planning to have a cannabis drug screen because EPIDIOLEX may affect your test results. Tell the person giving the drug test that you are taking EPIDIOLEX.

How should I take EPIDIOLEX?

- Read the Instructions for Use at the end of this Medication Guide for information on the right way to use EPIDIOLEX.
- Take EPIDIOLEX exactly as your healthcare provider tells you.
- Your healthcare provider will tell you how much EPIDIOLEX to take and when to take it.
- Measure each dose of EPIDIOLEX using the bottle adapter and the appropriate dosing syringes that come with EPIDIOLEX. If your dose of EPIDIOLEX is 1 mL or less, use the 1 mL syringes to take your medicine.
- Use a dry syringe each time you take EPIDIOLEX. If water is inside the syringe, it could cause the oil-based medicine to look cloudy.

What should I avoid while taking EPIDIOLEX?

- Do not drive, operate heavy machinery, or do other dangerous activities until you know how EPIDIOLEX affects you. EPIDIOLEX may cause you to feel sleepy.

What are the possible side effects of EPIDIOLEX?

EPIDIOLEX can cause serious side effects, including:

- See “What is the most important information I should know about EPIDIOLEX?”

The most common side effects of EPIDIOLEX include:

• sleepiness

• decreased appetite

• diarrhea

• increase in liver enzymes

• feeling very tired and weak

• rash

• sleep problems

• fever

• vomiting

• infections

These are not all of the possible side effects of EPIDIOLEX. For more information ask your healthcare provider or pharmacist.

Tell your healthcare provider about any side effect that bothers you or that does not go away.

Call your doctor for medical advice about side effects. You may report side effects to FDA at 1-800-FDA-1088.

You may also contact Jazz Pharmaceuticals at 1-800-520-5568.

How should I store EPIDIOLEX?

- Store EPIDIOLEX at room temperature between 68ºF to 77ºF (20ºC to 25ºC).
- Always store EPIDIOLEX in an upright position.
- Do not freeze.
- Keep the child-resistant cap tightly closed.
- Use EPIDIOLEX within 12 weeks of first opening the bottle. Throw away (dispose of) any unused medicine after 12 weeks.

Keep EPIDIOLEX and all medicines out of the reach of children.

General Information about the safe and effective use of EPIDIOLEX.

Medicines are sometimes prescribed for purposes other than those listed in a Medication Guide. Do not use EPIDIOLEX for a condition for which it was not prescribed. Do not give EPIDIOLEX to other people, even if they have the same symptoms that you have. It may harm them.

You can ask your pharmacist or healthcare provider for information about EPIDIOLEX that is written for health professionals.

What are the ingredients in EPIDIOLEX?

Active ingredient: cannabidiol
Inactive ingredients: dehydrated alcohol, sesame seed oil, strawberry flavor, and sucralose
EPIDIOLEX does not contain gluten (wheat, barley or rye).

Distributed by:
Jazz Pharmaceuticals, Inc.
Palo Alto, CA 94306
For more information, go to www.EPIDIOLEX.com or call 1-800-520-5568.
EPIDIOLEX® is a registered trademark of Jazz Pharmaceuticals plc or its subsidiaries.
© 2024 Jazz Pharmaceuticals, Inc.

This Medication Guide has been approved by the U.S. Food and Drug Administration Revised: 7/2025

INSTRUCTIONS FOR USE
EPIDIOLEX® (EH-peh-DYE-oh-lex)
(cannabidiol)
oral solution
100 mg/mL

Be sure that you read, understand and follow these instructions carefully to ensure proper dosing of the oral solution.

Important:

- Follow your healthcare provider’s instructions for the dose of EPIDIOLEX to take or give.
- Ask your healthcare provider or pharmacist if you are not sure how to prepare, take, or give the prescribed dose of EPIDIOLEX.
- Always use the oral syringe provided with EPIDIOLEX to make sure you measure the right amount of EPIDIOLEX.
- Do not use EPIDIOLEX after the expiration date on the package and each bottle.
- Use EPIDIOLEX within 12 weeks of first opening the bottle.
- After 12 weeks, safely throw away (dispose of) any EPIDIOLEX that has not been used.

Each package contains:

Child-resistant cap

2 Bottle adapters

1 bottle of EPIDIOLEX oral solution (100 mg/mL)

2 reusable 1 mL oral syringes and 2 reusable 5 mL oral syringes:

If your dose of EPIDIOLEX is 1 mL or less, use the 1 mL syringes to take your medicine.

For each syringe size:

- 1 syringe to take or give the dose of EPIDIOLEX
- 1 extra syringe (included as a spare if needed)

Note: If you lose or damage an oral syringe, or cannot read the markings, use the spare syringe.

Prepare The Bottle- to use EPIDIOLEX for the first time

1. Remove the child-resistant cap by pushing down while turning the cap to the left (counter-clockwise).

2. Push the bottle adapter firmly into the bottle. Make sure the bottle adapter is fully inserted. If not fully inserted, small parts such as the bottle adapter may become a choking hazard for children and pets.

Note: Do not remove the bottle adapter from the bottle after it is inserted.

Prepare The Dose

Your healthcare provider will tell you how much EPIDIOLEX to take or give.

3. Use this table to measure the total dose of EPIDIOLEX to be given.

Dose How to measure
1 mL or less Use the 1 mL oral syringe 1 time
More than 1 mL and less than 5 mL Use the 5 mL oral syringe 1 time
More than 5 mL Use the 5 mL oral syringe more than 1 time

4. Push the plunger all the way down and insert the tip of the oral syringe fully into the bottle adapter. With the oral syringe in place, turn the bottle upside down.

5. Slowly pull the plunger of the oral syringe to withdraw the dose of EPIDIOLEX needed. See Step 3 for how to measure the total dose of EPIDIOLEX.

Line up the end of the plunger with the marking for your dose of EPIDIOLEX.

What to do if you see air bubbles:

If there are air bubbles in the oral syringe, keep the bottle upside down and push the plunger so that all of the
liquid flows back into the bottle. Repeat Step 5 until the air bubbles are gone.

6. When you have measured the correct dose of EPIDIOLEX, leave the oral syringe in the bottle adapter and turn the bottle right side up.

7. Carefully remove the oral syringe from the bottle adapter.

Give EPIDIOLEX

8. Place the tip of the oral syringe against the inside of the cheek and gently push the plunger until all the EPIDIOLEX in the syringe is given.

Do not forcefully push on the plunger.

Do not direct the medicine to the back of the mouth or throat. This may cause choking.

If the dose of EPIDIOLEX prescribed by the healthcare provider is more than 5 mL, repeat steps 4 through 8 to complete the dose.

For example:
If your dose of EPIDIOLEX is 8 mL, withdraw 5 mL of medicine into the syringe and give the medicine.
Insert the tip of the oral syringe back into the bottle adapter and withdraw 3 mL of medicine. Give the
medicine to receive a total dose of 8 mL.

Clean Up

9. Screw the child-resistant cap back on the bottle tightly by turning the cap to the right (clockwise).

Do not remove the bottle adapter. The cap will fit over it.

10. Fill a cup with warm soapy water and clean the oral syringe by drawing water in and out of the syringe using the plunger.

11. Remove the plunger from the barrel of the oral syringe and rinse both parts under tap water.

Do not wash the oral syringe in the dishwasher.

12. Shake off any extra water from the plunger and oral syringe barrel, and allow them to air dry until next use.

Make sure the oral syringe is completely dry before the next use. If water is inside the syringe, it could cause the oil-based medicine to look cloudy.

Do not throw away the oral syringe.

How should I store EPIDIOLEX?

- Store EPIDIOLEX at room temperature between 68°F to 77°F (20°C to 25°C).
- Always store EPIDIOLEX in an upright position.
- Do not freeze.
- Keep the child-resistant cap tightly closed.
- Use EPIDIOLEX within 12 weeks of first opening the bottle. Dispose of any unused EPIDIOLEX after 12 weeks.
- Keep EPIDIOLEX and all medicines out of the reach of children.

Helpline Details

For additional assistance, call the toll-free helpline at 1-833-426-4243.

Hours:
Monday-Friday 08:00am – 08:00pm EST

Frequently Asked Questions

Q: What if there are air bubbles in the oral syringe?

A: Push the liquid back into the bottle and repeat Step 5 until the air bubbles are gone.

Q: What should I do if the liquid in the bottle has turned cloudy?

A: The liquid in the bottle may turn cloudy if water gets in the bottle. This does not change the safety or how well the medicine works. Continue to use the cloudy liquid as prescribed by your healthcare provider.
Always make sure the oral syringes are completely dry before each use.

Q: What should I do if the oral syringe is not completely dry before use?

A: If the oral syringe is not completely dry, use the spare syringe provided in the pack.

Distributed by:

Jazz Pharmaceuticals, Inc.
Palo Alto, CA 94306

EPIDIOLEX® is a registered trademark of Jazz Pharmaceuticals plc or its subsidiaries.
© 2023 Jazz Pharmaceuticals, Inc.

This Instructions for Use has been approved by the U.S. Food and Drug Administration.

Revised: 07/2025

PRINCIPAL DISPLAY PANEL

NDC 70127-100-01
EPIDIOLEX
(cannabidiol)
100 mg/mL
oral solution

PRINCIPAL DISPLAY PANEL

NDC 70127-100-10
EPIDIOLEX
(cannabidiol)
100 mg/mL
oral solution

PRINCIPAL DISPLAY PANEL

NDC 70127-100-06
EPIDIOLEX
(cannabidiol)
100 mg/mL
oral solution

PRINCIPAL DISPLAY PANEL

NDC 70127-100-60
EPIDIOLEX
(cannabidiol)
100 mg/mL
oral solution